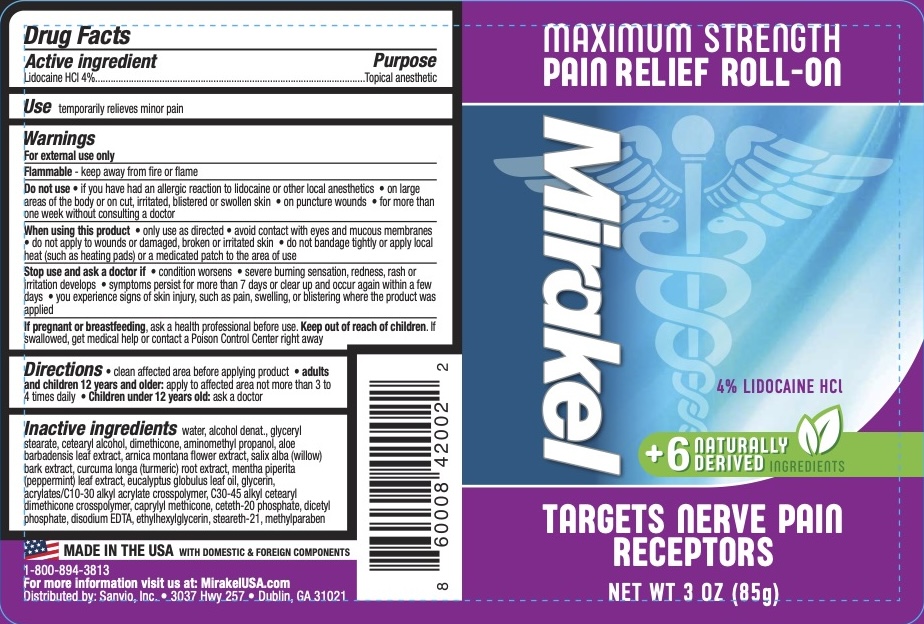 DRUG LABEL: Mirakel Pain Relief Roll-On
NDC: 78589-257 | Form: GEL
Manufacturer: Sanvio, Inc.
Category: otc | Type: HUMAN OTC DRUG LABEL
Date: 20240130

ACTIVE INGREDIENTS: LIDOCAINE HYDROCHLORIDE 4 g/100 g
INACTIVE INGREDIENTS: C30-45 ALKYL CETEARYL DIMETHICONE CROSSPOLYMER; CAPRYLYL TRISILOXANE; METHYLPARABEN; MENTHA PIPERITA LEAF; ALCOHOL; CETOSTEARYL ALCOHOL; WATER; GLYCERYL MONOSTEARATE; AMINOMETHYLPROPANOL; EUCALYPTUS OIL; ALOE VERA LEAF; STEARETH-21; GLYCERIN; ACRYLATES/C10-30 ALKYL ACRYLATE CROSSPOLYMER (60000 MPA.S); CETETH-20 PHOSPHATE; DIHEXADECYL PHOSPHATE; EDETATE DISODIUM; ETHYLHEXYLGLYCERIN; DIMETHICONE 200; ARNICA MONTANA FLOWER; SALIX ALBA BARK; TURMERIC

Mirakel Pain Relief Roll-On

ACTIVE INGREDIENT

Lidocaine HCl 4%

PURPOSE

Topical anesthetic

INDICATIONS AND USAGE

Temporarily relieves minor pain.

WARNINGS

For external use only.

Flammable--keep away from fire or flame.

Do not use

- if you have an allergic reaction to lidocaine or other local anesthetics
- on large areas of the body or on cut, irritated, blistered, or swollen skin
- on puncture wounds
- for more than one week without consulting a doctor

Stop use and ask a doctor if

- condition worsens
- severe burning sensation, redness, rash, or irritation develops
- symptoms persist for more than 7 days or clear p and occur again within a few days
- you experience signs of skin injury, such as pain, swelling, or blistering where the product was applied

PREGNANCY OR BREAST FEEDING

If pregnant or breastfeeding, ask a health professional before use.

KEEP OUT OF REACH OF CHILDREN

If swallowed, get medical help or contact a Poison Control Center right away.

DOSAGE AND ADMINISTRATION

Clean affected area before applying product. Adults and children 12 years and older: apply to the affected area not more than 3 to 4 times daily. Children under 12 years old: ask a doctor.

INACTIVE INGREDIENT

Water, Alcohol Denat., Glyceryl Stearate, Cetearyl Alcohol, Dimethicone, Aminomethyl Propanol, Aloe Barbadensis Leaf Extract, Arnica Montana Flower Extract, Salix Alba (Willow) Bark Extract, Curcuma Longa (Turmeric) Root Extract, Mentha Piperita (Peppermint) Leaf Extract, Eucalyptus Globulus Leaf Oil, Glycerin, Acrylates/C10-30 Alkyl Acrylate Crosspolymer, C30-45 Alkyl Cetearyl Dimethicone Crosspolymer, Caprylyl Methicone, Ceteth-20 Phosphate, Dicetyl Phosphate, Disodium EDTA, Ethylhexylglycerin, Steareth-21, Methylparaben